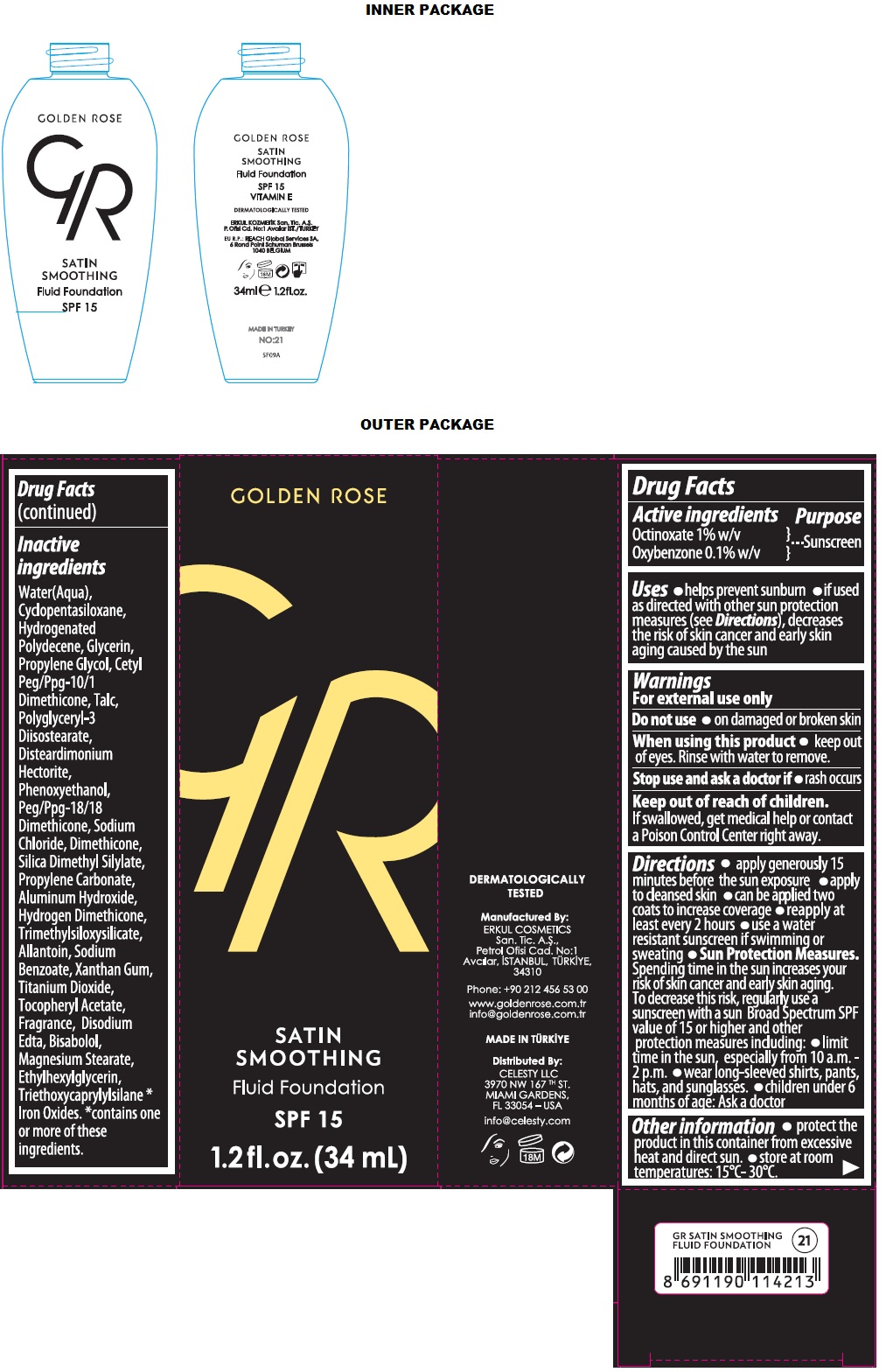 DRUG LABEL: GR SATIN SMOOTHING Fluid Foundation SPF 15
NDC: 82715-104 | Form: LIQUID
Manufacturer: ERKUL KOZMETIK SANAYI VE TICARET ANONIM SIRKETI
Category: otc | Type: HUMAN OTC DRUG LABEL
Date: 20250806

ACTIVE INGREDIENTS: OCTINOXATE 1 g/100 mL; OXYBENZONE 0.1 g/100 mL
INACTIVE INGREDIENTS: WATER; CYCLOMETHICONE 5; HYDROGENATED POLYDECENE (3100 CST); GLYCERIN; PROPYLENE GLYCOL; CETYL PEG/PPG-10/1 DIMETHICONE (HLB 4); TALC; POLYGLYCERYL-3 DIISOSTEARATE; DISTEARDIMONIUM HECTORITE; PHENOXYETHANOL; PEG/PPG-18/18 DIMETHICONE; SODIUM CHLORIDE; DIMETHICONE, UNSPECIFIED; SILICA DIMETHYL SILYLATE; PROPYLENE CARBONATE; ALUMINUM HYDROXIDE; HYDROGEN DIMETHICONE (13 CST); TRIMETHYLSILOXYSILICATE (M/Q 0.6-0.8); ALLANTOIN; SODIUM BENZOATE; XANTHAN GUM; TITANIUM DIOXIDE; .ALPHA.-TOCOPHEROL ACETATE; EDETATE DISODIUM ANHYDROUS; LEVOMENOL; MAGNESIUM STEARATE; ETHYLHEXYLGLYCERIN; TRIETHOXYCAPRYLYLSILANE; FERRIC OXIDE RED; FERRIC OXIDE YELLOW; FERROSOFERRIC OXIDE

GR GOLDEN ROSE SATIN SMOOTHING Fluid Foundation

Active ingredients

Octinoxate 1% w/v
Oxybenzone 0.1% w/v

Purpose

Sunscreen

Uses

• helps prevent sunburn • if used as directed with other sun protection measures (see Directions), decreases the risk of skin cancer and early skin aging caused by the sun

Warnings

For external use only

Do not use • on damaged or broken skin

When using this product • keep out of eyes. Rinse with water to remove.

Stop use and ask a doctor if • rash occurs

Keep out of reach of children. If swallowed, get medical help or contact a Poison Control Center right away.

Directions

• apply generously 15 minutes before the sun exposure • apply to cleansed skin • can be applied two coats to increase coverage • reapply at least every 2 hours • use a water resistant sunscreen if swimming or sweating • Sun Protection Measures. Spending time in the sun increases your risk of skin cancer and early skin aging. To decrease this risk, regularly use a sunscreen with a sun Broad Spectrum SPF value of 15 or higher and other protection measures including: • limit time in the sun, especially from 10 a.m. - 2 p.m. • wear long-sleeved shirts, pants, hats, and sunglasses. • children under 6 months of age: Ask a doctor

Other information

• protect the product in this container from excessive heat and direct sun. • store at room temperatures: 15°C- 30°C.

Inactive ingredients

Water(Aqua), Cyclopentasiloxane, Hydrogenated Polydecene, Glycerin, Propylene Gylcol, Cetyl Peg/Ppg-10/1 Dimethicone, Talc, Polyglyceryl-3 Diisostearate, Disteardimonium Hectorite, Phenoxyethanol, Peg/Ppg-18/18 Dimethicone, Sodium Chloride, Dimethicone, Silica Dimethyl Silylate, Propylene Carbonate, Aluminum Hydroxide, Hydrogen Dimethicone, Trimethylsiloxysilicate, Allantoin, Sodium Benzoate, Xanthan gum, Titanium Dioxide, Tocopheryl Acetate, Fragrance, Disodium Edta, Bisabolol, Magnesium Stearate, Ethylhexylglycerin, Triethoxycaprylylsilane *Iron Oxides. *contains one or more of these ingredients.

GOLDEN ROSE

SPF 15

VITAMIN E

DERMATOLOGICALLY TESTED

Manufactured By:
ERKUL COSMETICS San. Tic. A.Ş.,
Petrol Ofisi Cad. No:1
Avcılar, ISTANBUL, TURKIYE,
34310

Phone: +90 212 456 53 00

www.goldenrose.com.tr
info@goldenrose.com.tr

MADE IN TURKIYE

Distributed By:
CELESTY LLC
3970 NW 167TH ST.
MIAMI GARDENS,
FL 33054 – USA

info@celesty.com

EU R.P.: REACH Global Services SA,
6 Rond point Schuman Brussels
1040 BELGIUM

NO:21